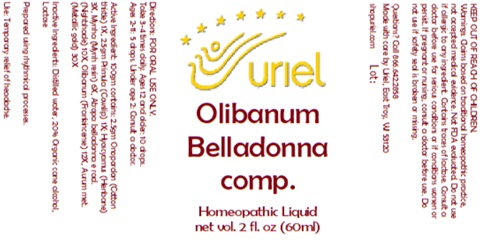 DRUG LABEL: Olibanum Belladonna comp.
NDC: 48951-7213 | Form: LIQUID
Manufacturer: Uriel Pharmacy, Inc
Category: homeopathic | Type: HUMAN OTC DRUG LABEL
Date: 20250124

ACTIVE INGREDIENTS: ONOPORDUM ACANTHIUM FLOWER 1 [hp_X]/1 mL; MYRRH 6 [hp_X]/1 mL; FRANKINCENSE 12 [hp_X]/1 mL; HYOSCYAMUS NIGER LEAF 3 [hp_X]/1 mL; ATROPA BELLADONNA 10 [hp_X]/1 mL; PRIMULA VERIS FLOWER 1 [hp_X]/1 mL; GOLD 30 [hp_X]/1 mL
INACTIVE INGREDIENTS: WATER; ALCOHOL; LACTOSE

Olibanum Belladonna comp.

INDICATIONS AND USAGE

Directions: FOR ORAL USE ONLY.

DOSAGE AND ADMINISTRATION

Take 3-4 times daily. Ages 12 and older: 10 drops.
Ages 2-11: 5 drops. Under age 2: Consult a doctor.

Active Ingredient: 100gm contains: 2.5gm Onopordon (Cotton thistle) 1X, 2.5gm Primula (Cowslip) 1X; Hyoscyamus (Henbane) 3X, Myrrha (Myrrh resin) 6X, Atropa belladonna e rad. (Nightshade) 10X, Olibanum (Frankincense) 12X, Aurum met. (Metallic gold) 30X

INACTIVE INGREDIENT

Inactive Ingredients: Distilled water, 20% Organic cane alcohol, Lactose

Prepared using rhythmical processes.

PURPOSE

Use: Temporary relief of headache.

KEEP OUT OF REACH OF CHILDREN.

WARNINGS

Warnings: Claims based on traditional homeopathic practice, not accepted medical evidence. Not FDA evaluated. Do not use if allergic to any ingredient. Contains traces of lactose. Consult a doctor before use for serious conditions or if conditions worsen or persist. If pregnant or nursing, consult a doctor before use. Do not use if safety seal is broken or missing.

Questions? Call 866.642.2858
Made with care by Uriel, East Troy, WI 53120
shopuriel.com Lot: